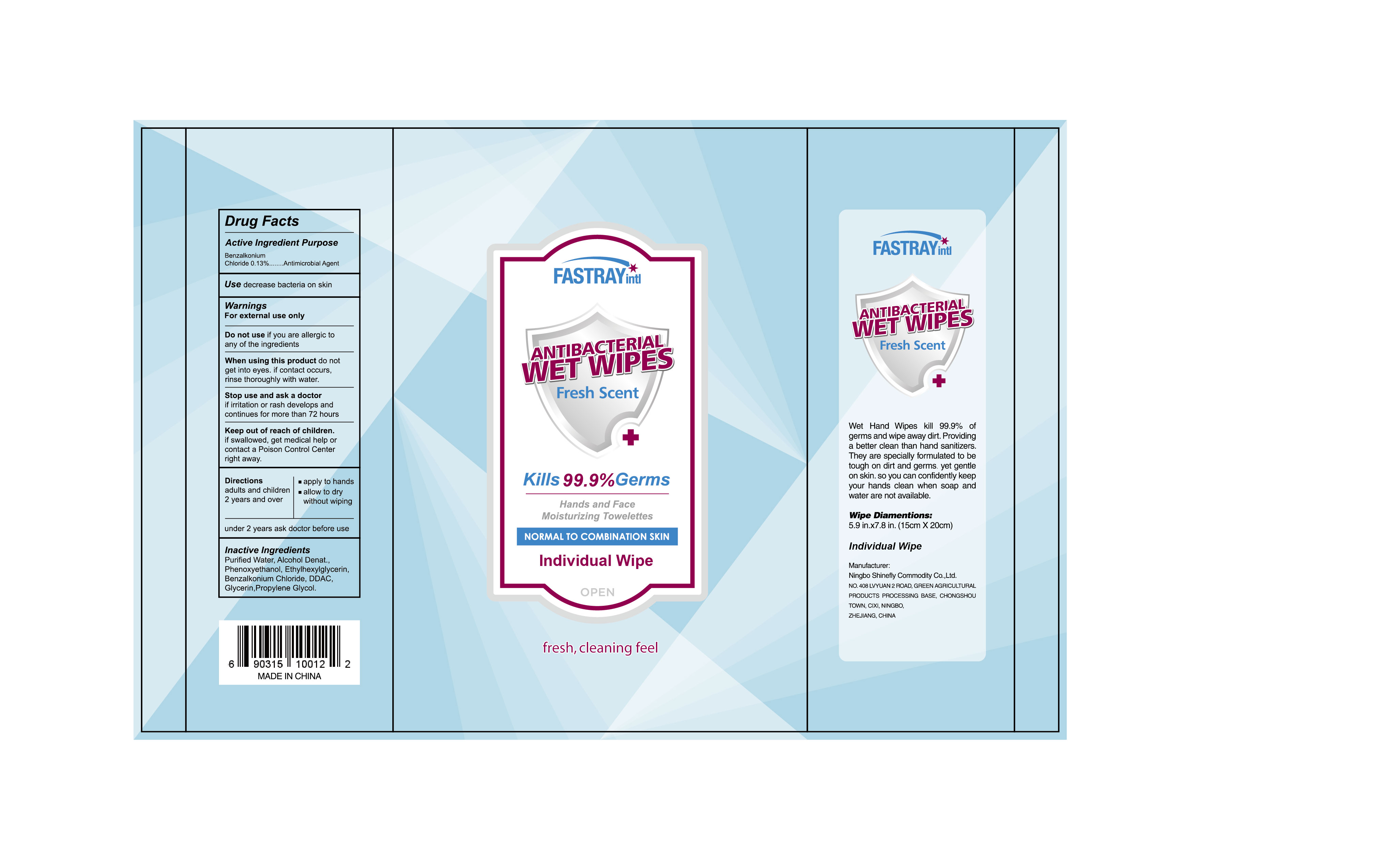 DRUG LABEL: FASTRAY intl Antibacterial WET WIPES
NDC: 75441-001 | Form: SOLUTION
Manufacturer: NINGBO SHINEFLY COMMODITY CO.,LTD.
Category: otc | Type: HUMAN OTC DRUG LABEL
Date: 20200415

ACTIVE INGREDIENTS: BENZALKONIUM CHLORIDE 0.00585 g/1 1
INACTIVE INGREDIENTS: ALCOHOL 0.1 g/1 1; ETHYLHEXYLGLYCERIN 0.001 g/1 1; PROPYLENE GLYCOL 0.001 g/1 1; FRAGRANCE LAVENDER & CHIA F-153480 0.001 g/1 1; WATER 0.8877 g/1 1; PHENOXYETHANOL 0.005 g/1 1; DIDECYLDIMONIUM CHLORIDE 0.002 g/1 1; GLYCERIN 0.001 g/1 1

The ANTIBACTERIAL WET WIPE is manufactured using only the following United States Pharmacopoeia (USP) grade ingredients in the preparation of the product (percentage in final product formulation) consistent with World Health Organization (WHO) recommendations.

a. The ANTIBACTERIAL WET WIPE is manufactured using only the following United States Pharmacopoeia (USP) grade ingredients in the preparation of the product (percentage in final product formulation) consistent with World Health Organization (WHO) recommendations

b. Phenoxyethanol 0.5 %
c. Ethylhexylglycerin 0.1 %
d. Didecyldimonium Chloride 0.2 %
e. Propylene Glycol 0.1 %
f. Glycerin 0.1 %
g.Fragrance 0.1 %
h. Alcohol Denat 10.0 %

i. water 88.77 %

Active Ingredient(s)

Benzalkonium Chloride 0.13%. Purpose: Antimicrobial Agent

PURPOSE

ANTIBACTERIAL:ANTIBACTERIAL WET WIPE

USE

ANTIBACTERIAL WET WIPE to decrease bacteria on skin

warnings

For external use only.

Do Not Use

if you are allergic to any of the ingredients.

when using this product

do not get into eyes.if contact occurs,rinse thoroughly with water.

stop use and ask a doctor

if irrigation or rash develops and continues for more than 72 hours

keep out of reach of children

if swallowed,get medical help or contact a Poison Control Center reght away.

Directions

- adults and children 2 years and over,under 2 years ask doctor before use.
- apply to hands
- allow to dry without wiping

other information

Wet Hand Wipes kill 99.9% of germs and wipe away dirt.Providing a better clean than hand sanitizers.They are specially formulated to be tough on dirt and germs.yet gentle on skin. so you can confidently keep your hands clean when soap and water are not available.

inactive ingredients

purified water, Phenoxyethanol, Ethylhexylglycerin, Didecyldimonium Chloride, Propylene

Glycol, Glycerin, Fragrance, Alcohol Denat

Package Label,Principal Display Panel

xP NDC: